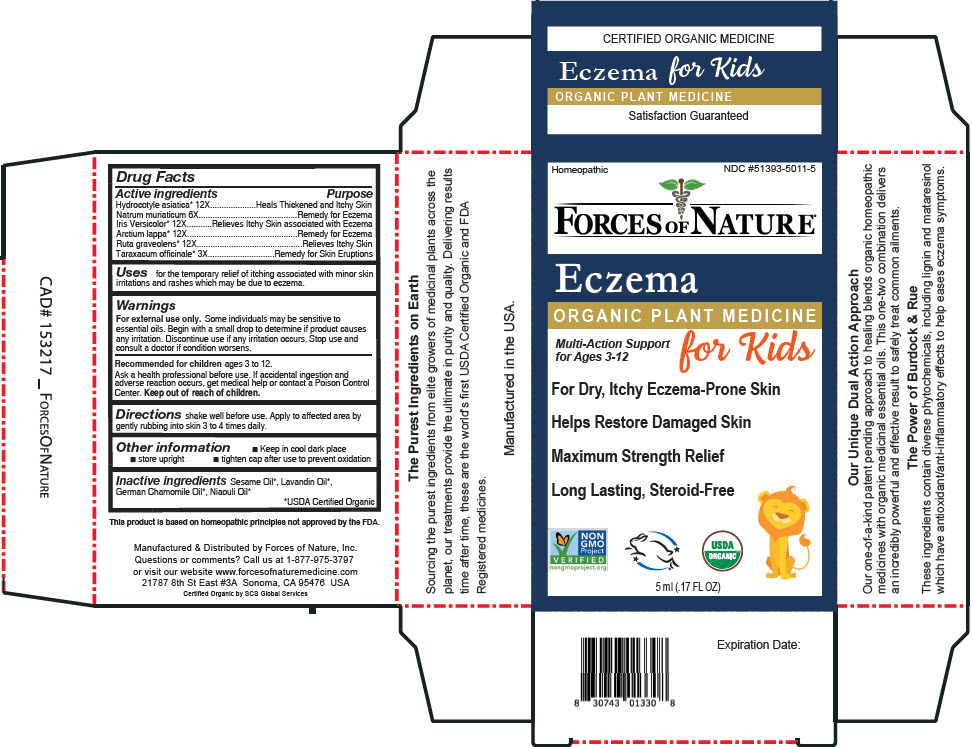 DRUG LABEL: Eczema Kids
NDC: 51393-5011 | Form: SOLUTION/ DROPS
Manufacturer: Forces of Nature
Category: homeopathic | Type: HUMAN OTC DRUG LABEL
Date: 20220930

ACTIVE INGREDIENTS: Centella Asiatica Whole 12 [hp_X]/100 mL; Sodium Chloride 6 [hp_X]/100 mL; Iris Versicolor Root 12 [hp_X]/100 mL; Arctium Lappa Root 12 [hp_X]/100 mL; Ruta Graveolens Whole 12 [hp_X]/100 mL; Taraxacum Officinale Root 3 [hp_X]/100 mL
INACTIVE INGREDIENTS: Sesame Oil; Lavandin Oil; CHAMOMILE FLOWER OIL; Niaouli Oil

Eczema Kids

Drug Facts

ACTIVE INGREDIENT

Active ingredients | Purpose
Hydrocotyle asiatica 12X | Heals Thickened and Itchy Skin
Natrum muriaticum 6X | Remedy for Eczema
Iris Versicolor [USDA Certified Organic] 12X | Relieves Itchy Skin associated with Eczema
Arctium lappa 12X | Remedy for Eczema
Ruta graveolens 12X | Relieves Itchy Skin
Taraxacum officinale 3X | Remedy for Skin Eruptions

Uses

for the temporary relief of itching associated with minor skin irritations and rashes which may be due to eczema.

Warnings

For external use only. Some individuals may be sensitive to essential oils. Begin with a small drop to determine if product causes any irritation. Discontinue use if any irritation occurs. Stop use and consult a doctor if condition worsens.

ASK DOCTOR/PHARMACIST

Recommended for children ages 3 to 12.

Ask a health professional before use. If accidental ingestion and adverse reaction occurs, get medical help or contact a Poison Control Center.

Keep out of reach of children.

Directions

shake well before use. Apply to affected area by gently rubbing into skin 3 to 4 times daily.

Other information

- Keep in cool dark place
- store upright
- tighten cap after use to prevent oxidation

Inactive ingredients

Sesame Oil, Lavandin Oil, German Chamomile Oil, Niaouli Oil

Questions or comments?

Call us at 1-877-975-3797 or visit our website www.forcesofnaturemedicine.com

Manufactured & Distributed by Forces of Nature, Inc.
21787 8th St East #3A Sonoma, CA 95476 USA

PRINCIPAL DISPLAY PANEL - 5 ml Bottle Carton

Homeopathic

NDC #51393-5011-5

FORCES OF NATURE®

Eczema

ORGANIC PLANT MEDICINE

Multi-Action Support
for Ages 3-12

for Kids

For Dry, Itchy Eczema-Prone Skin

Helps Restore Damaged Skin

Maximum Strength Relief

Long Lasting, Steroid-Free

NON
GMO
Project
VERIFIED
nongmoproject.org

USDA
ORGANIC

5 ml (.17 FL OZ)